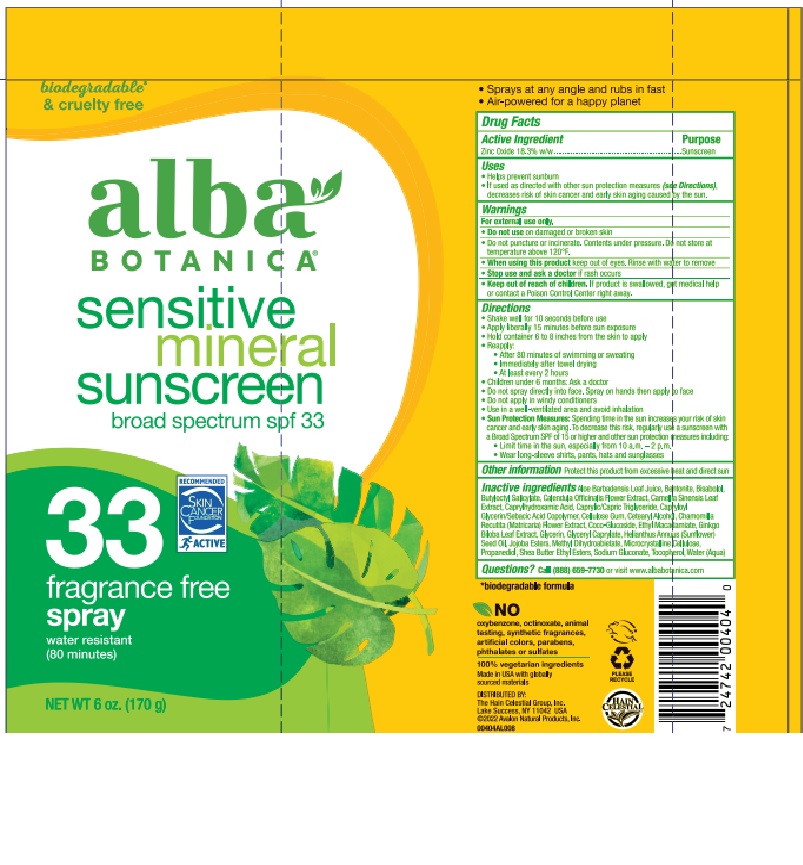 DRUG LABEL: Alba Botanica Sensitive Mineral Sunscreen SPF 33
NDC: 61995-3033 | Form: AEROSOL
Manufacturer: The Hain Celestial Group, Inc.
Category: otc | Type: HUMAN OTC DRUG LABEL
Date: 20241128

ACTIVE INGREDIENTS: ZINC OXIDE 18.3 g/100 g
INACTIVE INGREDIENTS: .ALPHA.-TOCOPHEROL; CAMELLIA SINENSIS FLOWER; MATRICARIA CHAMOMILLA FLOWERING TOP OIL; HYDROLYZED JOJOBA ESTERS (ACID FORM); SODIUM GLUCONATE; WATER; GLYCERIN; SUNFLOWER OIL; PROPANEDIOL; COCO GLUCOSIDE; CELLULOSE, MICROCRYSTALLINE; .BETA.-BISABOLOL; CAPRYLHYDROXAMIC ACID; CAPRYLOYL GLYCERIN/SEBACIC ACID COPOLYMER (2000 MPA.S); METHYL DIHYDROABIETATE; ALOE VERA LEAF; BENTONITE; CARBOXYMETHYLCELLULOSE; CETYL ALCOHOL; BUTYLOCTYL SALICYLATE; ETHYL MACADAMIATE; CALENDULA OFFICINALIS FLOWER; PEG-4 CAPRYLIC/CAPRIC GLYCERIDES; GINKGO BILOBA LEAF OIL; GLYCERYL CAPRYLATE; SHEA BUTTER ETHYL ESTERS

Alba Botanica Sensitive Mineral Sunscreen SPF 33

ACTIVE INGREDIENT

Zinc Oxide 18.3% (w/w)

DOSAGE AND ADMINISTRATION

Apply liberally 15 minutes before sun exposure. Reapply: ● after 80 minutes of swimming or sweating ● immediately after towel drying ● at least every 2 hours. Children under 6 months of age: ask a doctor.

PURPOSE

Sunscreen

WARNINGS

For external use only. Do not use on damaged or broken skin. When using this product keep out of eyes. Rinse with water to remove. Stop use and ask a doctor if skin rash occurs.

Keep out of reach of children. If swallowed get medical help or contact Poison Center right away.

INACTIVE INGREDIENT

Aloe Barbadensis Leaf Juice, Bentonite, Bisabolol, Butyloctyl Salicylate, Calendula Officinalis Flower Extract, Camellia Sinensis Leaf Extract, Caprylhydroxamic Acid, Caprylic/Capric Triglyceride, Capryloyl Glycerin/Sebacic Acid Copolymer, Cellulose Gum, Cetearyl Alcohol, Chamomilla Recutita (Matricaria) Flower Extract, Coco-Glucoside, Ethyl Macadamiate, Ginkgo Biloba Leaf Extract, Glycerin, Glyceryl Caprylate, Helianthus Annuus (Sunflower) Seed Oil, Jojoba Esters, Methyl Dihydroabietate, Microcrystalline Cellulose, Propanediol, Shea Butter Ethyl Esters, Sodium Gluconate, Tocopherol, Water (Aqua)

INDICATIONS AND USAGE

Helps prevents sunburns. If used as directed with other sun protection measures, decreases risk of skin cancer and early skin aging caused by sun exposure. Skin Protection Measures: Spending time in the sun increases your risk of skin cancer and early skin aging. To decrease risk, regularly use sunscreen with Broad Spectrum SPF 15 or higher and other protective measures including: limit time in sun, especially from10am to 2pm, and wear long sleeved shirts, pants, hats and sunglases.